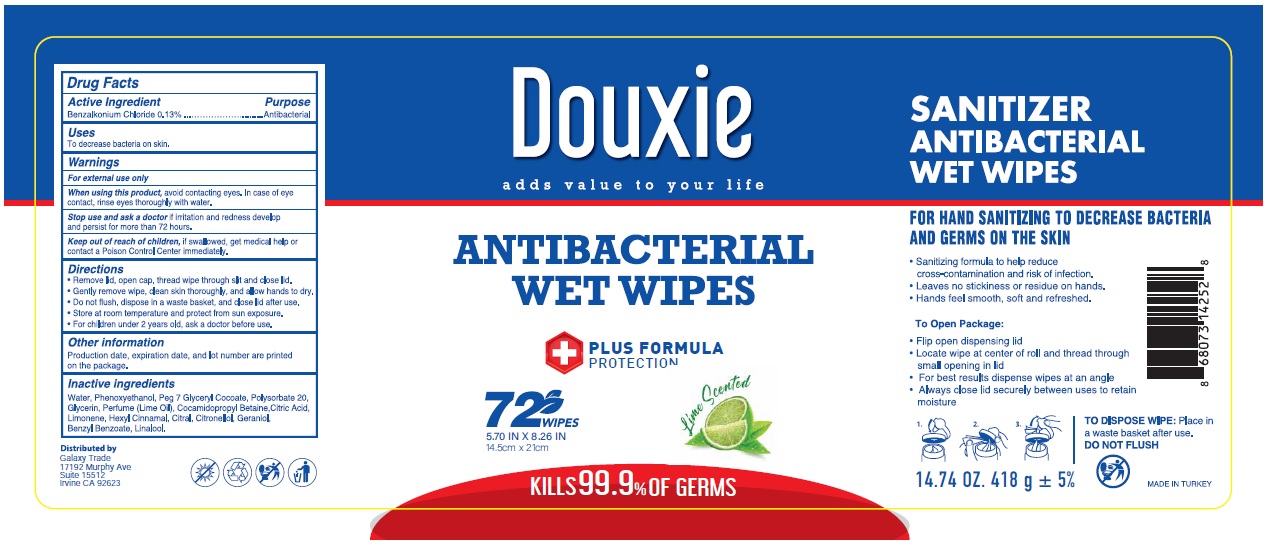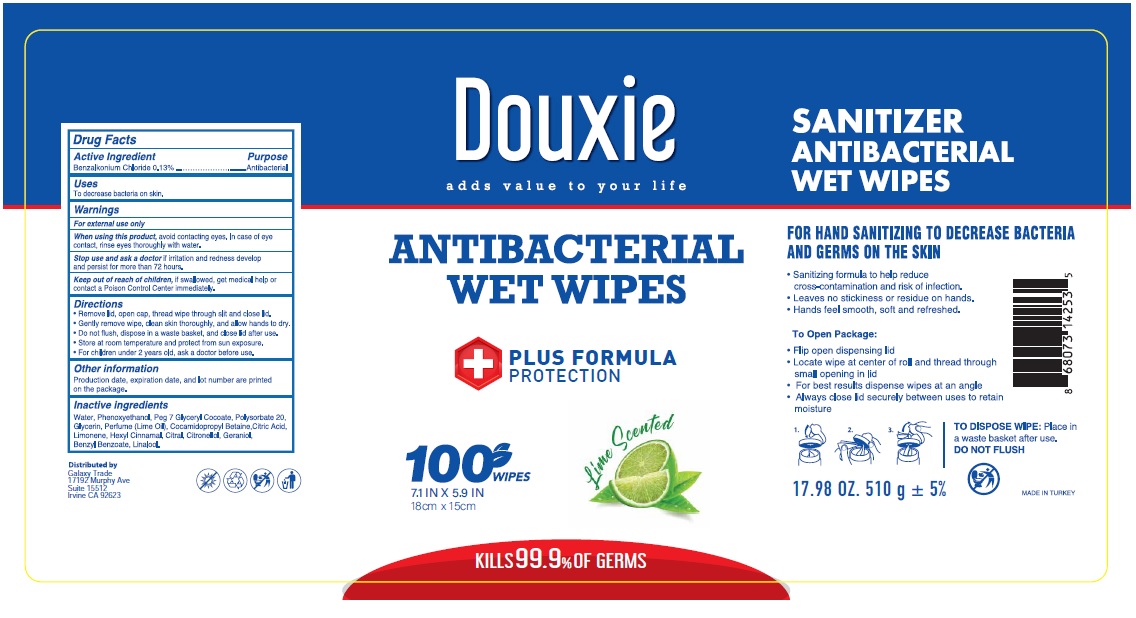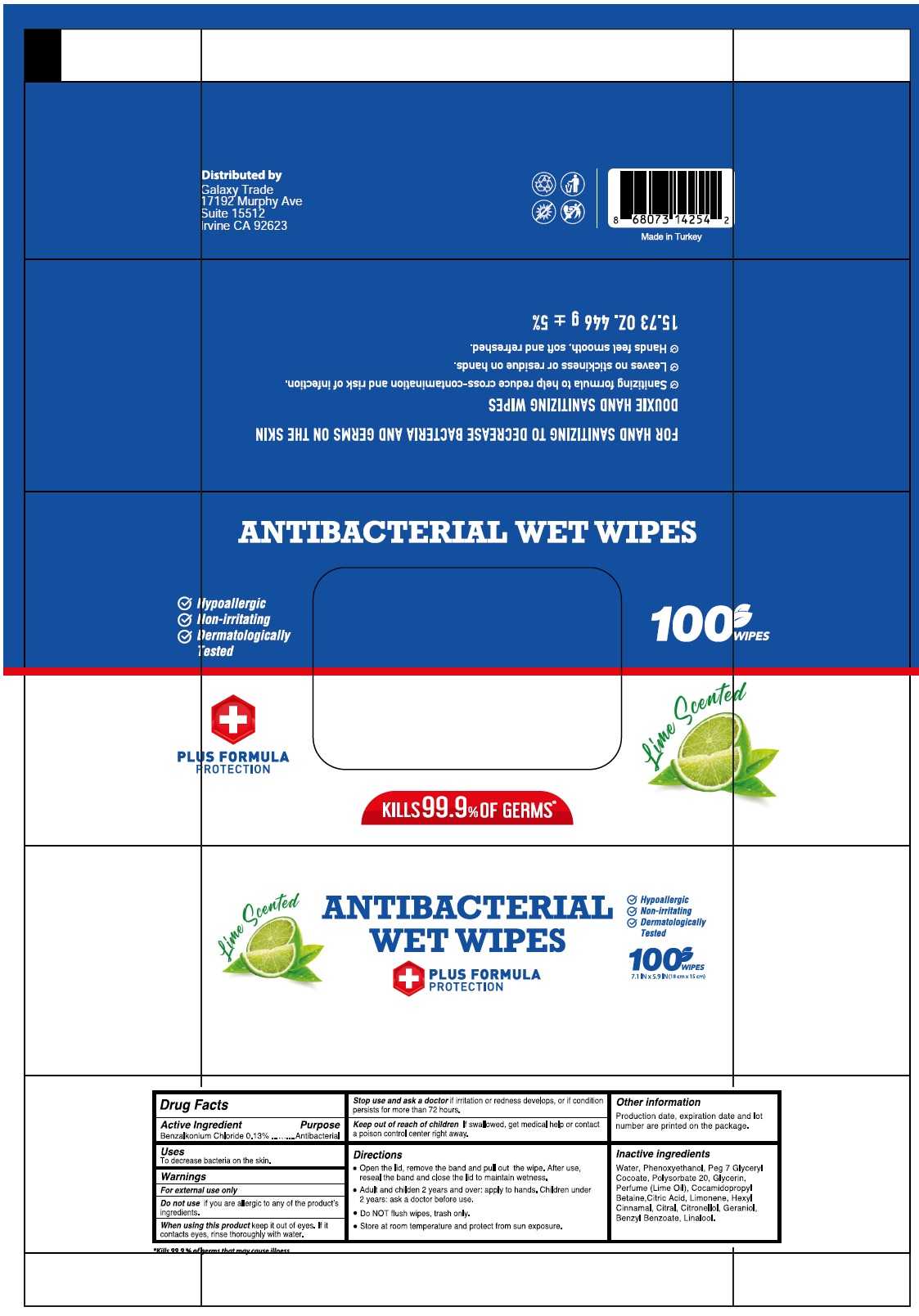 DRUG LABEL: Douxie ANTIBACTERIAL WET WIPES
NDC: 78089-049 | Form: CLOTH
Manufacturer: Endeks Kimya Sanayi Ve Ticaret Anonim Sirketi
Category: otc | Type: HUMAN OTC DRUG LABEL
Date: 20201128

ACTIVE INGREDIENTS: BENZALKONIUM CHLORIDE 0.13 g/100 mL
INACTIVE INGREDIENTS: WATER; PHENOXYETHANOL; PEG-7 GLYCERYL COCOATE; POLYSORBATE 20; GLYCERIN; LIME OIL; COCAMIDOPROPYL BETAINE; CITRIC ACID MONOHYDRATE; LIMONENE, (+)-; .ALPHA.-HEXYLCINNAMALDEHYDE; CITRAL; .BETA.-CITRONELLOL, (R)-; GERANIOL; BENZYL BENZOATE; LINALOOL, (+/-)-

Douxie ANTIBACTERIAL WET WIPES

Active Ingredient

Benzalkonium Chloride 0.13%

Purpose

Antibacterial

Uses

To decrease bacteria on the skin.

Warnings

For external use only

Do not use if you are allergic to any of the product's ingredients

When using this product keep it out of eyes. If it contacts eyes, rinse thoroughly with water.

Stop use and ask a doctor if irritation and redness develops, or if condition persists for more than 72 hours.

Keep out of reach of children If swallowed, get medical help or contact a poison control center right away.

Directions

• Open the lid, remove the band and pull out the wipe. After use, reseal the band and close the lid to maintain wetness.

• Adult and children 2 years and over: apply to hands. Children under 2 years: ask a doctor before use.

• Do NOT flush wipes, trash only.

• Store at room temperature and protect from sun exposure.

Other information

Production date, expiration date, and lot number are printed on the package.

Inactive ingredients

Water, Phenoxyethanol, Peg 7 Glyceryl Cocoate, Polysorbate 20, Glycerin, Perfume (Lime Oil), Cocamidopropyl Betaine, Citric Acid, Limonene, Hexyl Cinnamal, Citral, Citronellol, Geraniol, Benzyl Benzoate, Linalool.

+ PLUS FORMULA PROTECTION

Lime Scented

KILLS 99.9% OF GERMS*

*Kills 99.9% of germs that may cause illness

• Hypoallergic

• Non-irritating

• Dermatologically Tested
FOR HAND SANITIZING TO DECREASE BACTERIA AND GERMS ON THE SKIN

DOUXIE HAND SANITIZING WIPES

• Sanitizing formula to help reduce cross-contamination and risk of infection.

• Leaves no stickiness or residue on hands.

• Hands feel smooth, soft and refreshed.
Distributed by

Galaxy Trade

17192 Murphy Ave

Suite 15512

Irvine CA 92623

Made in Turkey